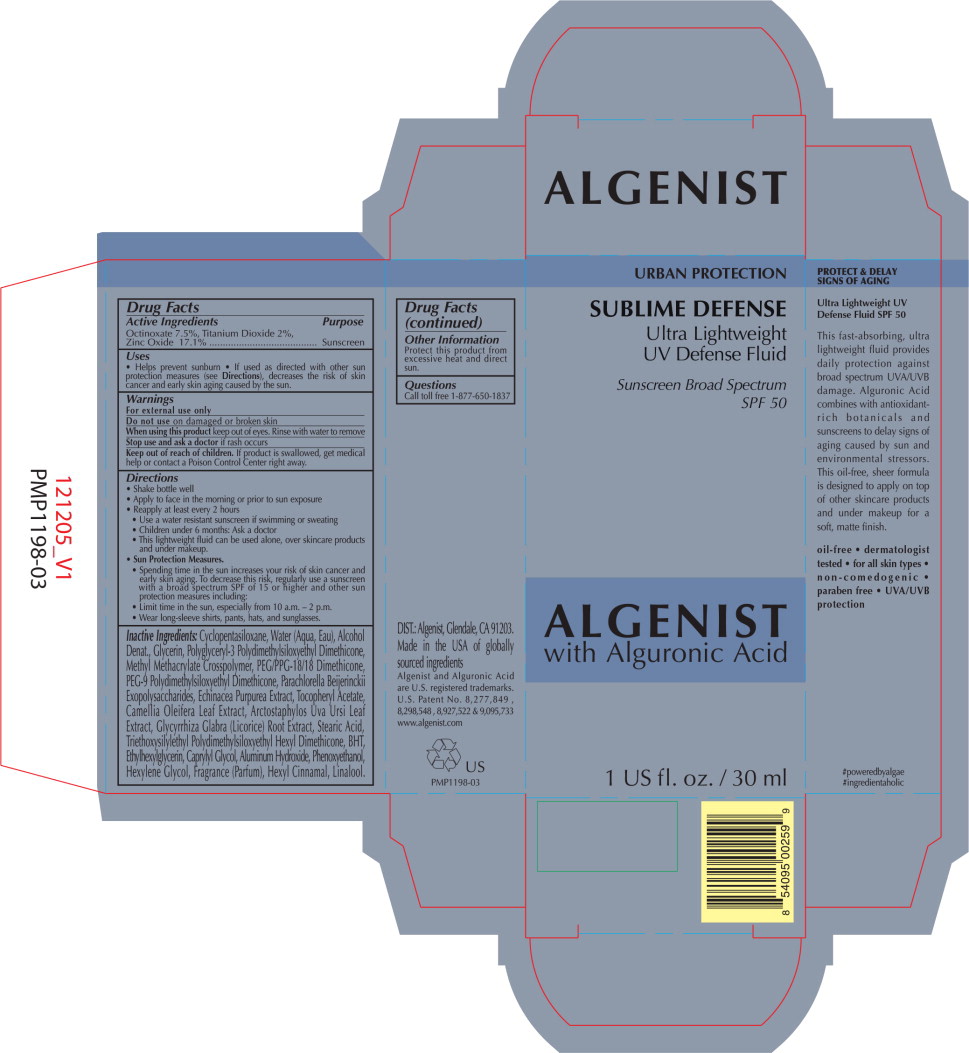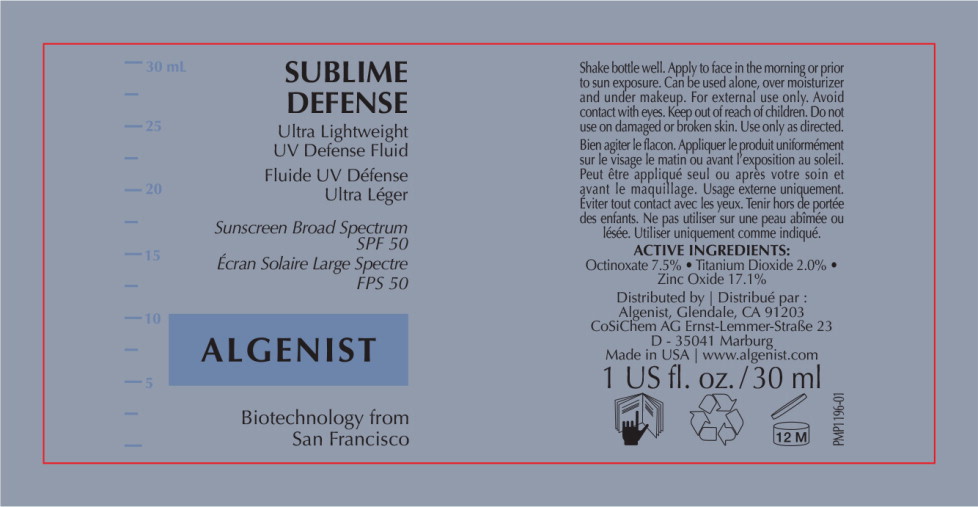 DRUG LABEL: Algenist

NDC: 53407-138 | Form: CREAM
Manufacturer: Solazyme, Inc.
Category: otc | Type: HUMAN OTC DRUG LABEL
Date: 20250422

ACTIVE INGREDIENTS: Octinoxate
 75 mg/1 mL; Titanium Dioxide
 20 mg/1 mL; Zinc Oxide
 171 mg/1 mL
INACTIVE INGREDIENTS: CYCLOMETHICONE 5; water; alcohol; glycerin; METHYL METHACRYLATE; peg/ppg-18/18 dimethicone; echinacea purpurea; .ALPHA.-TOCOPHEROL ACETATE; camellia oleifera seed; ARCTOSTAPHYLOS UVA-URSI LEAF; GLYCYRRHIZA GLABRA; stearic acid; ethylhexylglycerin; caprylyl glycol; aluminum hydroxide; phenoxyethanol; hexylene glycol

Drug Facts

Active Ingredients

Octinoxate 7.5%, Titanium Dioxide 2%, Zinc Oxide 17.1%

Purpose

Sunscreen

Uses

- Helps prevent sunburn
- If used as directed with other sun protection measures (see Directions), decreases the risk of skin cancer and early skin aging caused by the sun.

Warnings

For external use only

Do not use on damaged or broken skin

When using this product keep out of eyes. Rinse with water to remove

Stop use and ask a doctor if rash occurs

Keep out of reach of children. If product is swallowed, get medical help or contact a Poison Control Center right away.

Directions

- Shake bottle well
- Apply to face in the morning or prior to sun exposure
- Reapply at least every 2 hours
  - Use a water resistant sunscreen if swimming or sweating
  - Children under 6 months: Ask a doctor
  - This lightweight fluid can be used alone, over skincare products and under makeup.
- Sun Protection Measures.
  - Spending time in the sun increases your risk of skin cancer and early skin aging. To decrease this risk, regularly use a sunscreen with a broad spectrum SPF of 15 or higher and other sun protection measures including:
  - Limit time in the sun, especially from 10 a.m. – 2 p.m.
  - Wear long-sleeve shirts, pants, hats, and sunglasses.

Inactive Ingredients:

Cyclopentasiloxane, Water (Aqua, Eau), Alcohol Denat., Glycerin, Polyglyceryl-3 Polydimethylsiloxyethyl Dimethicone, Methyl Methacrylate Crosspolymer, PEG/PPG-18/18 Dimethicone, PEG-9 Polydimethylsiloxyethyl Dimethicone, Parachlorella Beijerinckii Exopolysaccharides, Echinacea Purpurea Extract, Tocopheryl Acetate, Camellia Oleifera Leaf Extract, Arctostaphylos Uva Ursi Leaf Extract, Glycyrrhiza Glabra (Licorice) Root Extract, Stearic Acid, Triethoxysilylethyl Polydimethylsiloxyethyl Hexyl Dimethicone, BHT, Ethylhexylglycerin, Caprylyl Glycol, Aluminum Hydroxide, Phenoxyethanol, Hexylene Glycol, Fragrance (Parfum), Hexyl Cinnamal, Linalool.

Other Information

Protect this product from excessive heat and direct sun.

Questions

Call toll free 1-877-650-1837

Principal Display Panel – 30 mL Carton Label

URBAN PROTECTION

SUBLIME DEFENSE

Ultra Lightweight
UV Defense Fluid

Sunscreen Broad Spectrum
SPF 50

ALGENIST
with Alguronic Acid

1 US fl. oz. / 30 ml

Principal Display Panel – 30 mL Jar Label

SUBLIME
DEFENSE

Ultra Lightweight
UV Defense Fluid

Fluide UV Défense
Ultra Léger

Sunscreen Broad Spectrum
SPF 50

Écran Solaire Large Spectre
FPS 50

ALGENIST

Biotechnology from
San Francisco